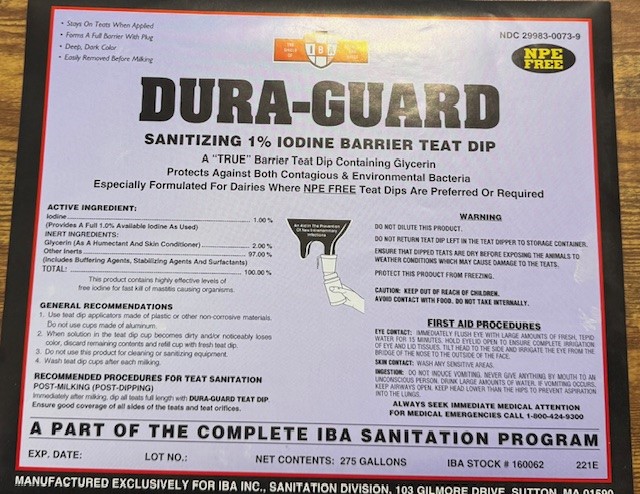 DRUG LABEL: DURA-GUARD NPE FREE
NDC: 29983-0073 | Form: SOLUTION
Manufacturer: IBA
Category: animal | Type: OTC ANIMAL DRUG LABEL
Date: 20241226

ACTIVE INGREDIENTS: IODINE 10 g/1 L
INACTIVE INGREDIENTS: XANTHAN GUM; SODIUM LAURYL GLYCOL CARBOXYLATE

DURA-GUARD Sanitizing 1% Iodine Barrier Teat Dip A "TRUE" Barrier Teat Dip Containing Glycerin Protects Against Both Contagious & Environmental Bacteria
Especially Formulated For Dairies Where NPE FREE Teat Dips are Preferred or Required

ACTIVE INGREDIENT

Iodine ....1.00% (Provides 1.0% minimum Titratable Iodine)
Inert Ingredients:
Skin Conditioners...........2.0%
Other Inerts................97.00%
(Includes Buffering Agents and Surfactants)
Total........100.00%
pH of 5.5 at time of manufacture

This product contains highly effective levels of free iodine for fast kill of mastitis causing organisms

INDICATIONS AND USAGE

GENERAL RECOMMENDATIONS
1. Use teat dip applicators made of plastic or other non-corrosive materials. Do not use cups made of aluminum.
2. When solution in the teat dip cup becomes dirty and/or noticeably loses color, discard remaining contents and refill cup with fresh teat dip.
3. Do not use this product for cleaning or sanitizing equipment
4. Wash Teat Dip cups after each milking.

RECOMMENDED PROCEDURES FOR TEAT SANITATION

POST-MILKING (POST DIPPING)
Immediately after milking dip all teats full length with DURA-GUARD Teat Dip Ensure good coverage of all sides of the teats and teat orifices.

WARNINGS AND PRECAUTIONS

WARNING
DO NOT DILUTE THIS PRODUCT
DO NOT RETURN TEAT DIP LEFT IN THE TEAT DIPPER TO STORAGE CONTAINER.
ENSURE THAT DIPPED TEATS ARE DRY BEFORE EXPOSING THE ANIMALS TO WEATHER CONDITIONS WHICH MAY CAUSE DAMAGE TO THE TEATS.
PROTECT THIS PRODUCT FROM FREEZING.

EYE CONTACT: IMMEDIATELY FLUSH EYE WITH LARGE AMOUNTS OF FRESH, TEPID WATER FOR 15 MINUTES. HOLD EYELID OPEN TO ENSURE COMPLETE IRRIGATION OF EYE AND LID TISSUES. TILT HEAD TO THE SIDE AND IRRIGATE THE EYE FROM THE BRIDGE OF THE NOSE TO THE OUTSIDE OF THE FACE.
SKIN CONTACT: WASH ANY SENSITIVE AREAS.
INGESTION: DO NOT INDUCE VOMITING. NEVER GIVE ANYTHING BY MOUTH TO AN UNCONSCIOUS PERSON. DRINK LARGE AMOUNTS OF WATER. IF VOMITING OCCURS KEEP AIRWAYS OPEN. KEEP HEAD LOWER THAN THE HIPS TO PREVENT ASPIRATION INTO THE LUNGS.

ALWAYS SEEK IMMEDIATE MEDICAL ATTENTION FOR MEDICAL EMERGENCIES CALL 1-800-424-9300